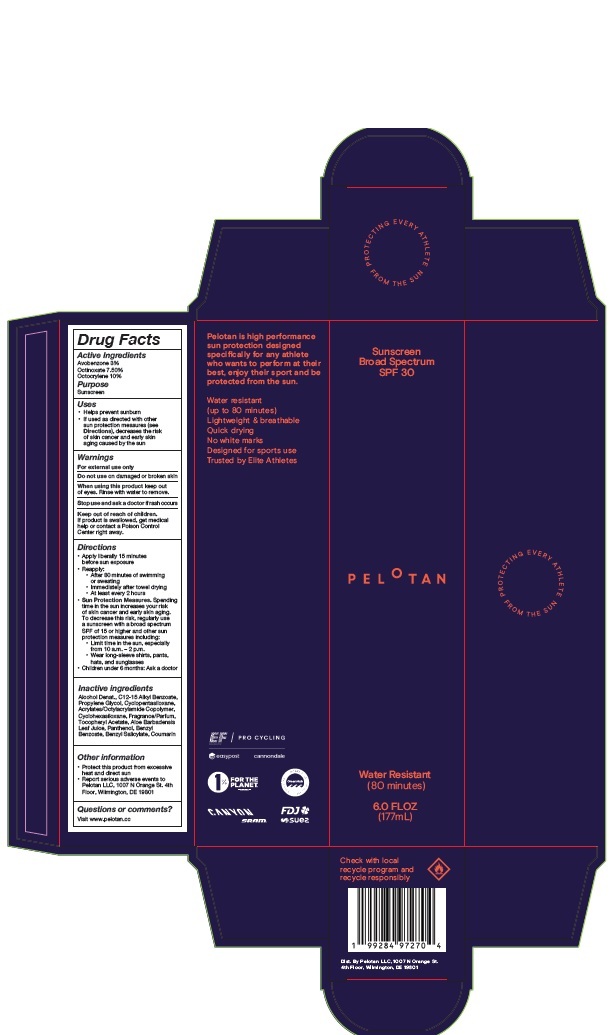 DRUG LABEL: Pelotan Sunscreen Broad Spectrum SPF 30
NDC: 85962-001 | Form: SPRAY
Manufacturer: Pelotan LLC
Category: otc | Type: HUMAN OTC DRUG LABEL
Date: 20250723

ACTIVE INGREDIENTS: OCTINOXATE 75 mg/1 mL; AVOBENZONE 30 mg/1 mL; OCTOCRYLENE 100 mg/1 mL
INACTIVE INGREDIENTS: PROPYLENE GLYCOL; ALPHA-TOCOPHEROL ACETATE; PANTHENOL; ALOE VERA LEAF; CYCLOHEXASILOXANE; C12-15 ALKYL BENZOATE; ACRYLATES/OCTYLACRYLAMIDE COPOLYMER (40000 MW); BENZYL BENZOATE; COUMARIN; ALCOHOL; BENZYL SALICYLATE; CYCLOPENTASILOXANE

Pelotan Sunscreen Broad Spectrum SPF 30 Spray

Active Ingredients

Avobenzone 3%

Octinoxate 7.50%

Octocrylene 10%

Purpose

Sunscreen

Uses

- Helps prevent sunburn
- If used as directed with other sun protection measures (see Directions), decreases the risk of skin cancer and early skin aging caused by the sun

Warnings

For external use only

Do not use

on damaged or broken skin

When using this product

keep out of eyes. Rinse with water to remove.

Stop use and ask a doctor

if rash occurs

Keep out of reach of children.

If product is swallowed, get medical help or contact a Poison Control Center right away.

Directions

- Apply liberally 15 minutes before sun exposure
- Reapply:
- After 80 minutes of swimming or sweating
- Immediately after towel drying
- At least every 2 hours
- Sun Protection Measures. Spending time in the sun increases your risk of skin cancer and early skin aging. To decrease this risk, regularly use a sunscreen with a broad spectrum SPF of 15 or higher and other sun protection measures including:
- Limit time in the sun, especially from 10 a.m. - 2 p.m.
- Wear long-sleeve shirts, pants, hats, and sunglasses
- Children under 6 months: Ask a doctor

Inactive ingredients

Alcohol Denat., C12-15 Alkyl Benzoate, Propylene Glycol, Cyclopentasiloxane, Acrylates/Octylacrylamide Copolymer, Cyclohexasiloxane, Fragrance/Parfum, Tocopheryl Acetate, Aloe Barbadensis Leaf Juice, Panthenol, Benzyl Benzoate, Benzyl Salicylate, Coumarin

Other information

- Protect this product from excessive heat and direct sun
- Report serious adverse events to Pelotan LLC, 1007 N Orange St. 4th Floor, Wilmington, DE 19801

Questions or comments?

Visit www.pelotan.cc